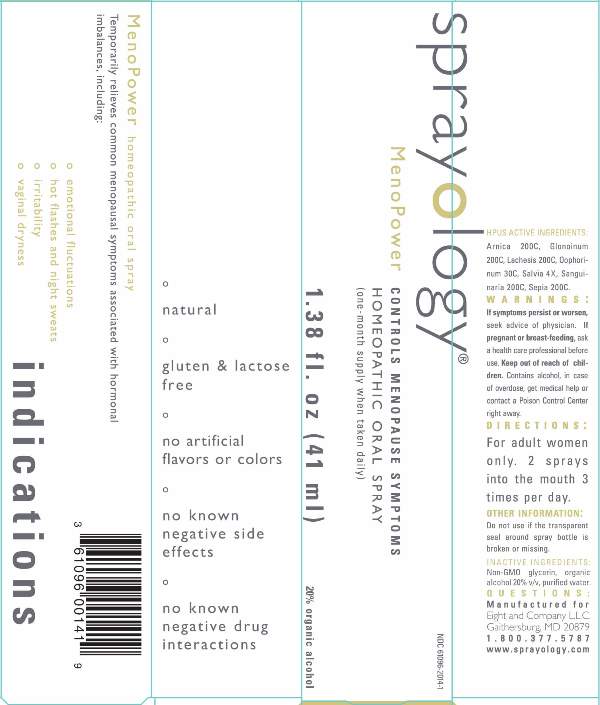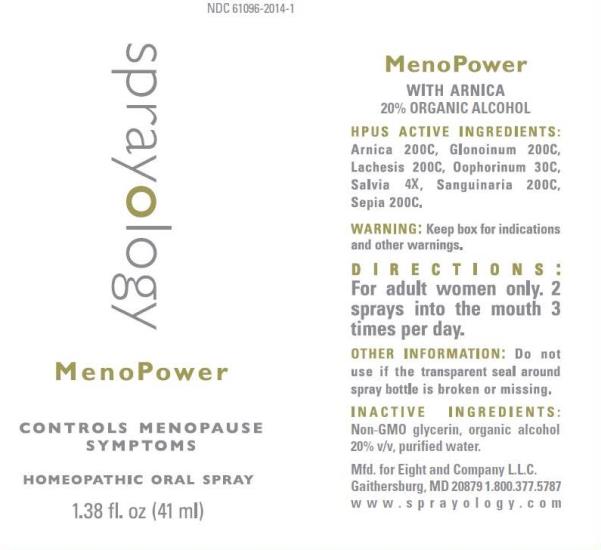 DRUG LABEL: MenoPower
NDC: 61096-2014 | Form: LIQUID
Manufacturer: Eight and Company L.L.C
Category: homeopathic | Type: HUMAN OTC DRUG LABEL
Date: 20251218

ACTIVE INGREDIENTS: ARNICA MONTANA WHOLE 200 [hp_C]/41 mL; NITROGLYCERIN 200 [hp_C]/41 mL; LACHESIS MUTA VENOM 200 [hp_C]/41 mL; SUS SCROFA OVARY 30 [hp_C]/41 mL; SAGE 4 [hp_X]/41 mL; SANGUINARIA CANADENSIS ROOT 200 [hp_C]/41 mL; SEPIA OFFICINALIS JUICE 200 [hp_C]/41 mL
INACTIVE INGREDIENTS: GLYCERIN; ALCOHOL; WATER

MenoPower

ACTIVE INGREDIENTS:

Arnica 200C, Glonoinum 200C, Lachesis 200C, Oophorinum 30C, Salvia 4X, Sanguinaria 200C, Sepia 200C

PURPOSE:

Temporarily relieves common menopausal symptoms associated with hormonal imbalances, including:

- emotional fluctuations
- hot flashes and night sweats
- irritability
- vaginal dryness

WARNINGS:

If symptoms persist or worsen, seek advice of physician. If pregnant or breast-feeding, ask a health care professional before use. Keep out of reach of children. Contains alcohol, in case of overdose, get medical help or contact a Poison Control Center right away.

Keep out of reach of children. Contains alcohol, in case of overdose, get medical help or contact a Poison Control Center right away.

DIRECTIONS:

For adult women only. 2 sprays into the mouth 3 times per day.

OTHER INFORMATION:

Do not use if the transparent seal around spray bottle is broken or missing.

INDICATIONS:

Temporarily relieves common menopausal symptoms associated with hormonal imbalances, including:

° emotional fluctuations

° hot flashes and night sweats

° irritability

° vaginal dryness

° natural

° gluten & lactose free

° no artificial flavors or colors

° no known negative side effects

° no known negative drug interactions

INACTIVE INGREDIENTS:

Non-GMO glycerin, v/v, organic alcohol 20% v/v and purified water.

QUESTIONS:

Mfd. for Eight and Company L.L.C.

Gaithersburg, MD 20879 1.800.377.5787

www.sprayology.com

PACKAGE LABEL DISPLAY:

NDC 61096-2014-1

sprayology

Menopower

CONTROLS MENOPAUSE SYMPTOMS

HOMEOPATHIC ORAL SPRAY

1.38 fl.oz (41 ml)